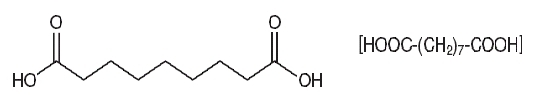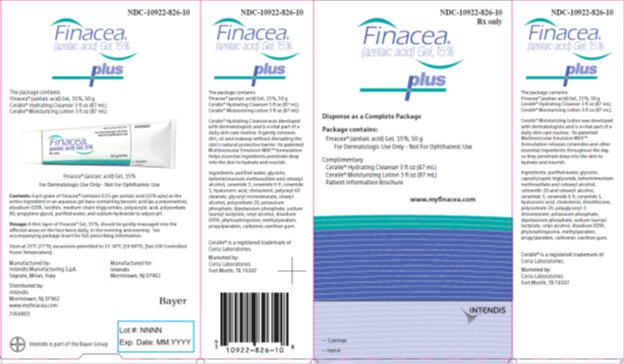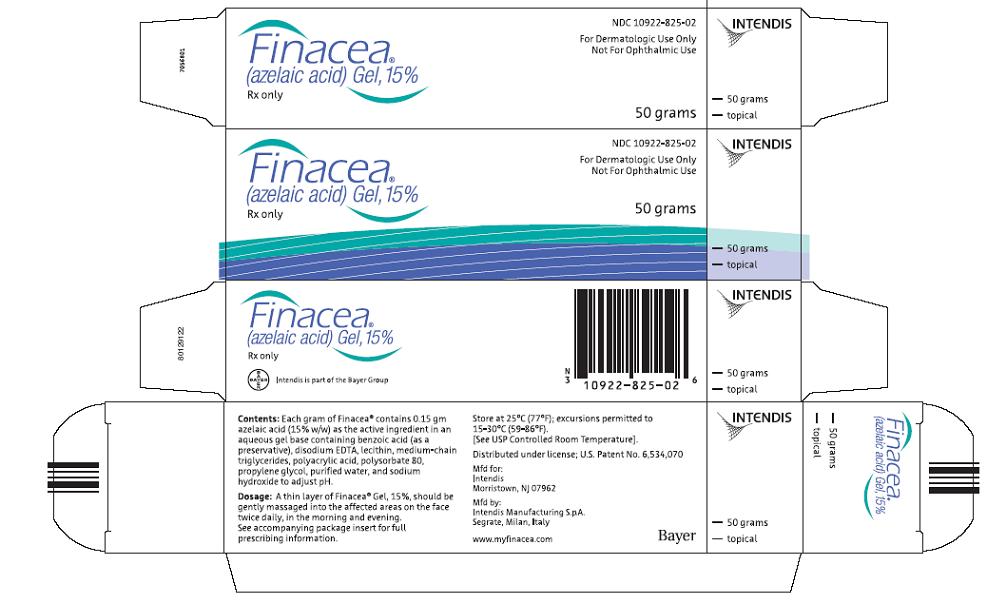 DRUG LABEL: Finacea
NDC: 10922-825 | Form: GEL
Manufacturer: Intendis Inc.
Category: prescription | Type: HUMAN PRESCRIPTION DRUG LABEL
Date: 20110412

ACTIVE INGREDIENTS: AZELAIC ACID 0.15 g/1 g
INACTIVE INGREDIENTS: BENZOIC ACID; EDETATE DISODIUM; 1,2-DIARACHIDOYL-SN-GLYCERO-3-PHOSPHOCHOLINE; MEDIUM-CHAIN TRIGLYCERIDES; POLYACRYLIC ACID (250000 MW); POLYSORBATE 80; PROPYLENE GLYCOL; SODIUM HYDROXIDE; WATER

Finacea®
(azelaic acid) Gel, 15%

For Dermatologic Use Only-Not for Ophthalmic, Oral, or Intravaginal Use

Rx only

DESCRIPTION

FINACEA® (azelaic acid) Gel, 15%, contains azelaic acid, a naturally occurring saturated dicarboxylic acid. Chemically, azelaic acid is 1,7-heptanedicarboxylic acid, with the molecular formula C9 H16 O4, a molecular weight of 188.22, and the structural formula:

Azelaic acid is a white, odorless crystalline solid that is poorly soluble in water at 20°C (0.24%), but freely soluble in boiling water and in ethanol.

Each gram of FINACEA Gel, 15%, contains 0.15 gm azelaic acid (15% w/w) as the active ingredient in an aqueous gel base containing benzoic acid (as a preservative), disodium EDTA, lecithin, medium-chain triglycerides, polyacrylic acid, polysorbate 80, propylene glycol, purified water, and sodium hydroxide to adjust pH.

CLINICAL PHARMACOLOGY

The mechanism(s) by which azelaic acid interferes with the pathogenic events in rosacea are unknown.

Pharmacokinetics:

The percutaneous absorption of azelaic acid after topical application of FINACEA Gel, 15%, could not be reliably determined. Mean plasma azelaic acid concentrations in rosacea patients treated with FINACEA Gel, 15%, twice daily for at least 8 weeks are in the range of 42 to 63.1 ng/mL. These values are within the maximum concentration range of 24.0 to 90.5 ng/mL observed in rosacea patients treated with vehicle only. This indicates that FINACEA Gel, 15%, does not increase plasma azelaic acid concentration beyond the range derived from nutrition and endogenous metabolism.

In vitro and human data suggest negligible cutaneous metabolism of ^3H-azelaic acid 20% cream after topical application. Azelaic acid is mainly excreted unchanged in the urine, but undergoes some ß-oxidation to shorter chain dicarboxylic acids.

CLINICAL STUDIES

FINACEA Gel, 15%, was evaluated for the treatment of mild to moderate papulopustular rosacea in 2 clinical trials comprising a total of 664 (333 active to 331 vehicle) patients. Both trials were multicenter, randomized, double-blind, vehicle-controlled 12-week studies with identical protocols. Overall, 92.5% of patients were Caucasian and 73% of patients were women, and the mean age was 49 (range 21 to 86) years. Enrolled patients had mild to moderate rosacea with a mean lesion count of 18 (range 8 to 60) inflammatory papules and pustules. Subjects without papules and pustules, with nodules, rhinophyma, or ocular involvement, and a history of hypersensitivity to propylene glycol or to any other ingredients of the study drug were excluded. FINACEA Gel, 15%, or its vehicle were to be applied twice daily for 12 weeks; no other topical or systemic medication affecting the course of rosacea and/or evaluability was to be used during the studies. Patients were instructed to avoid spicy foods, thermally hot foods and drinks, and alcoholic beverages during the study, and to use only very mild soaps or soapless cleansing lotion for facial cleansing.

The primary efficacy endpoints were both

1. change from baseline in inflammatory lesion counts and
2. success defined as a score of clear or minimal with at least a 2 step reduction from baseline on the Investigator's Global Assessment (IGA):

CLEAR: | No papules and/or pustules; no or residual erythema; no or mild to moderate telangiectasia
MINIMAL: | Rare papules and/or pustules; residual to mild erythema; mild to moderate telangiectasia
MILD: | Few papules and/or pustules; mild erythema; mild to moderate telangiectasia
MILD TO MODERATE: | Distinct number of papules and/or pustules; mild to moderate erythema; mild to moderate telangiectasia
MODERATE: | Pronounced number of papules and/or pustules; moderate erythema; mild to moderate telangiectasia
MODERATE TO SEVERE: | Many papules and/or pustules, occasionally with large inflamed lesions; moderate erythema; moderate degree of telangiectasia
SEVERE: | Numerous papules and/or pustules, occasionally with confluent areas of inflamed lesions; moderate or severe erythema; moderate or severe telangiectasia

Primary efficacy assessment was based on the intent-to-treat (ITT) population with last observation carried forward (LOCF).

Both studies demonstrated a statistically significant difference in favor of FINACEA Gel, 15%, over its vehicle in reducing the number of inflammatory papules and pustules associated with rosacea (Table 1) and with success on the IGA in the ITT-LOCF population at the end of treatment.

Table 1. Inflammatory Papules and Pustules (ITT population) [ITT population with last observation carried forward (LOCF);]
 | Study One; FINACEA Gel,15%; N = 164 | Study One; VEHICLE; N = 165 | Study Two; FINACEA Gel,15%; N = 167 | Study Two; VEHICLE; N = 166
Mean Lesion; Count; Baseline | 17.5 | 17.6 | 17.9 | 18.5
End of; Treatment | 6.8 | 10.5 | 9.0 | 12.1
Mean Percent; Reduction; End of; Treatment | 57.9% | 39.9% | 50.0% | 38.2%

Although some reduction of erythema which was present in patients with papules and pustules of rosacea occurred in clinical studies, efficacy for treatment of erythema in rosacea in the absence of papules and pustules has not been evaluated.

FINACEA Gel, 15%, was superior to the vehicle with regard to success based on the investigator's global assessment of rosacea on a 7-point static score at the end of treatment, (ITT population; Table 2).

Table 2. Investigator's Global Assessment at the End of Treatment [ITT population with last observation carried forward (LOCF);]
 | Study One; FINACEA Gel, 15%; N = 164 | Study One; VEHICLE; N = 165 | Study Two; FINACEA Gel, 15%; N = 167 | Study Two; VEHICLE; N = 166
CLEAR, MINIMAL; or MILD at End; of Treatment; (%of Patients) | 61% | 40% | 61% | 48%

INDICATIONS AND USAGE

FINACEA Gel, 15%, is indicated for topical treatment of inflammatory papules and pustules of mild to moderate rosacea. Although some reduction of erythema which was present in patients with papules and pustules of rosacea occurred in clinical studies, efficacy for treatment of erythema in rosacea in the absence of papules and pustules has not been evaluated. Patients should be instructed to avoid spicy foods, thermally hot foods and drinks, alcoholic beverages and to use only very mild soaps or soapless cleansing lotion for facial cleansing.

CONTRAINDICATIONS

FINACEA Gel, 15%, is contraindicated in individuals with a history of hypersensitivity to propylene glycol or any other component of the formulation.

WARNINGS

FINACEA Gel, 15%, is for dermatologic use only, and not for ophthalmic, oral or intravaginal use.

There have been isolated reports of hypopigmentation after use of azelaic acid. Since azelaic acid has not been well studied in patients with dark complexion, these patients should be monitored for early signs of hypopigmentation.

PRECAUTIONS

General:

Contact with the eyes should be avoided. If sensitivity or severe irritation develops with the use of FINACEA Gel, 15%, treatment should be discontinued and appropriate therapy instituted.

In a transgenic mouse study, chronic use of FINACEA Gel led to an increased number of animals with papillomas at the treatment site (see PRECAUTIONS: Carcinogenesis, Mutagenesis, and Impairment of Fertility). The clinical relevance of the findings in animal studies to humans is not clear.

Information for Patients

Patients using FINACEA Gel, 15%, should receive the following information and instructions:

- FINACEA Gel, 15%, is to be used only as directed by the physician.
- FINACEA Gel, 15%, is for external use only. It is not to be used orally, intravaginally, or for the eyes.
- Cleanse affected area(s) with a very mild soap or a soapless cleansing lotion and pat dry with a soft towel before applying FINACEA Gel, 15%. Avoid alcoholic cleansers, tinctures and astringents, abrasives and peeling agents.
- Avoid contact of FINACEA Gel, 15%, with the mouth, eyes and other mucous membranes. If it does come in contact with the eyes, wash the eyes with large amounts of water and consult a physician if eye irritation persists.
- The hands should be washed following application of FINACEA Gel, 15%.
- Cosmetics may be applied after FINACEA Gel, 15%, has dried.
- Skin irritation (e.g., pruritus, burning, or stinging) may occur during use of FINACEA Gel, 15%, usually during the first few weeks of treatment. If irritation is excessive or persists, use of FINACEA Gel, 15%, should be discontinued, and patients should consult their physician (see ADVERSE REACTIONS).
- Avoid any foods and beverages that might provoke erythema, flushing, and blushing (including spicy food, alcoholic beverages, and thermally hot drinks, including hot coffee and tea).
- Patients should report abnormal changes in skin color to their physician.
- Avoid the use of occlusive dressings or wrappings.

Drug Interactions:

There have been no formal studies of the interaction of FINACEA Gel, 15%, with other drugs.

Carcinogenesis, Mutagenesis, Impairment of Fertility:

Systemic long-term animal studies have not been performed to evaluate the carcinogenic potential of azelaic acid. In a 26-week dermal carcinogenicity study using transgenic (Tg.AC) mice, FINACEA Gel, 15%, and the gel vehicle, when applied once or twice daily, did not increase the number of female Tg.AC animals with papillomas at the treatment site. No statistically significant increase in the number of animals with papillomas at the treatment site was observed in male Tg.AC animals after once daily application. After twice daily application, FINACEA Gel, 15%, and the gel vehicle induced a statistically significant increase in the number of male animals with papillomas at the treatment site when compared to untreated males. This suggests that the positive effect may be associated with the vehicle application. The clinical relevance of the findings in animals to humans is not clear.

Azelaic acid was not mutagenic or clastogenic in a battery of in vitro (Ames assay, HGPRT in V79 cells {Chinese hamster lung cells}, and chromosomal aberration assay in human lymphocytes) and in vivo (dominant lethal assay in mice and mouse micronucleus assay) genotoxicity tests.

Oral administration of azelaic acid at dose levels up to 2500 mg/kg/day (162 times the maximum recommended human dose based on body surface area) did not affect fertility or reproductive performance in male or female rats.

Pregnancy:

Teratogenic Effects

Pregnancy Category B

There are no adequate and well-controlled studies of topically administered azelaic acid in pregnant women. The experience with FINACEA Gel, 15%, when used by pregnant women is too limited to permit assessment of the safety of its use during pregnancy.

Dermal embryofetal developmental toxicology studies have not been performed with azelaic acid, 15%, gel. Oral embryofetal developmental studies were conducted with azelaic acid in rats, rabbits, and cynomolgus monkeys. Azelaic acid was administered during the period of organogenesis in all three animal species. Embryotoxicity was observed in rats, rabbits, and monkeys at oral doses of azelaic acid that generated some maternal toxicity. Embryotoxicity was observed in rats given 2500 mg/kg/day (162 times the maximum recommended human dose based on body surface area), rabbits given 150 or 500 mg/kg/day (19 or 65 times the maximum recommended human dose based on body surface area) and cynomolgus monkeys given 500 mg/kg/day (65 times the maximum recommended human dose based on body surface area) azelaic acid. No teratogenic effects were observed in the oral embryofetal developmental studies conducted in rats, rabbits and cynomolgus monkeys.

An oral peri- and post-natal developmental study was conducted in rats. Azelaic acid was administered from gestational day 15 through day 21 postpartum up to a dose level of 2500 mg/kg/day. Embryotoxicity was observed in rats at an oral dose that generated some maternal toxicity (2500 mg/kg/day; 162 times the maximum recommended human dose based on body surface area). In addition, slight disturbances in the postnatal development of fetuses was noted in rats at oral doses that generated some maternal toxicity (500 and 2500 mg/kg/day; 32 and 162 times the maximum recommended human dose based on body surface area). No effects on sexual maturation of the fetuses were noted in this study.

Because animal reproduction studies are not always predictive of human response, this drug should be used only if clearly needed during pregnancy.

Nursing Mothers:

Equilibrium dialysis was used to assess human milk partitioning in vitro. At an azelaic acid concentration of 25 μg/mL, the milk/ plasma distribution coefficient was 0.7 and the milk/buffer distribution was 1.0, indicating that passage of drug into maternal milk may occur. Since less than 4% of a topically applied dose of azelaic acid cream, 20%, is systemically absorbed, the uptake of azelaic acid into maternal milk is not expected to cause a significant change from baseline azelaic acid levels in the milk. However, caution should be exercised when FINACEA Gel, 15%, is administered to a nursing mother.

Pediatric Use:

Safety and effectiveness of FINACEA Gel, 15%, in pediatric patients have not been established.

Geriatric Use:

Clinical studies of FINACEA Gel, 15%, did not include sufficient numbers of subjects aged 65 and over to determine whether they respond differently from younger subjects.

ADVERSE REACTIONS

Overall, treatment related adverse events, including burning, stinging/tingling, dryness/tightness/scaling, itching, and erythema/irritation/redness, were 19.4% (24/124) for FINACEA Gel, 15%, and 7.1% (9/127) for the active comparator gel at 15 weeks.

In two vehicle controlled, and one active controlled U.S. clinical studies, treatment safety was monitored in 788 patients who used twice daily FINACEA Gel, 15%, for 12 weeks (N=333) or for 15 weeks (N=124), or the gel vehicle (N=331) for 12 weeks.

Table 3. Cutaneous Adverse Events Occurring in ≥1% of Subjects in the Rosacea Trials by Treatment Group and Maximum Intensity [Subjects may have >1 cutaneous adverse event; thus, the sum of the frequencies of preferred terms may exceed the number of subjects with at least 1 cutaneous adverse event.]
 | FINACEA Gel, 15%; N=457 (100%) |  |  | Vehicle; N=331 (100%)
 | Mild; n=99; (22%) | Moderate; n=61; (13%) | Severe; n=27; (6%) | Mild; n=46; (14%) | Moderate; n=30; (9%) | Severe; n=5; (2%)
Burning/; stinging/; tingling | 71 (16%) | 42 (9%) | 17 (4%) | 8 (2%) | 6 (2%) | 2 (1%)
Pruritus | 29 (6%) | 18 (4%) | 5 (1%) | 9 (3%) | 6 (2%) | 0 (0%)
Scaling/dry; skin/xerosis | 21 (5%) | 10 (2%) | 5 (1%) | 31 (9%) | 14 (4%) | 1 (<1%)
Erythema/; irritation | 6 (1%) | 7 (2%) | 2 (<1%) | 8 (2%) | 4 (1%) | 2 (1%)
Contact; dermatitis | 2 (<1%) | 3 (1%) | 0 (0%) | 1 (<1%) | 0 (0%) | 0 (0%)
Edema | 3 (1%) | 2 (<1%) | 0 (0%) | 3 (1%) | 0 (0%) | 0 (0%)
Acne | 3 (1%) | 1 (<1%) | 0 (0%) | 1 (<1%) | 0 (0%) | 0 (0%)

FINACEA Gel, 15%, and its vehicle caused irritant reactions at the application site in human dermal safety studies. FINACEA Gel, 15%, caused significantly more irritation than its vehicle in a cumulative irritation study. Some improvement in irritation was demonstrated over the course of the clinical studies, but this improvement might be attributed to subject dropouts. No phototoxicity or photoallergenicity were reported in human dermal safety studies.

In patients using azelaic acid formulations, the following additional adverse experiences have been reported rarely: worsening of asthma, vitiligo depigmentation, small depigmented spots, hypertrichosis, reddening (signs of keratosis pilaris), and exacerbation of recurrent herpes labialis.

Post-marketing safety-Skin: facial burning and irritation; Eyes: iridocyclitis on accidental exposure with FINACEA Gel, 15%, to the eye (see PRECAUTIONS).

OVERDOSAGE

FINACEA Gel, 15%, is intended for cutaneous use only. If pronounced local irritation occurs, patients should be directed to discontinue use and appropriate therapy should be instituted (See PRECAUTIONS).

DOSAGE AND ADMINISTRATION

A thin layer of FINACEA Gel, 15%, should be gently massaged into the affected areas on the face twice daily, in the morning and evening. Patients should be reassessed if no improvement is observed upon completing 12 weeks of therapy.

HOW SUPPLIED

FINACEA Gel, 15%, is supplied in tubes in the following size:

FINACEA Gel, 15% – 50 g tube – NDC 10922-825-02

Storage

Store at 25°C (77°F); excursions permitted between 15–30°C (59–86°F) [see USP Controlled Room Temperature].

Distributed under license; U.S. Patent No 6,534,070

www.myfinacea.com

© 2010, Intendis, Inc. All rights reserved. July 2010

Manufactured by Intendis Manufacturing S.p.A., Segrate, Milan, Italy

Distributed by:

Intendis
Morristown, NJ 07962

Intendis is part of the Bayer Group

6706803

PACKAGE/LABEL PRINCIPAL DISPLAY PANEL

Finacea plus

NDC 10922-826-10
Rx only
Finacea (azelaic acid) Gel, 15%–Plus

Dispense as a Complete Package
Package contains: Finacea® (azelaic acid) Gel, 15%, 50 g
For Dermatologic Use Only - Not For Ophthalmic Use

Complimentary CeraVe® Hydrating Cleanser 3 fl oz (87 mL)
CeraVe® Moisturizing Lotion 3 fl oz (87 mL)
Patient Information Brochure

www.myfinacea.com

PACKAGE LABEL

Finacea Gel, 15%–50 g Tube

NDC 10922-825-02

For Dermatologic Use Only
Not For Ophthalmic Use

Finacea®
(azelaic acid) Gel 15%

50 grams